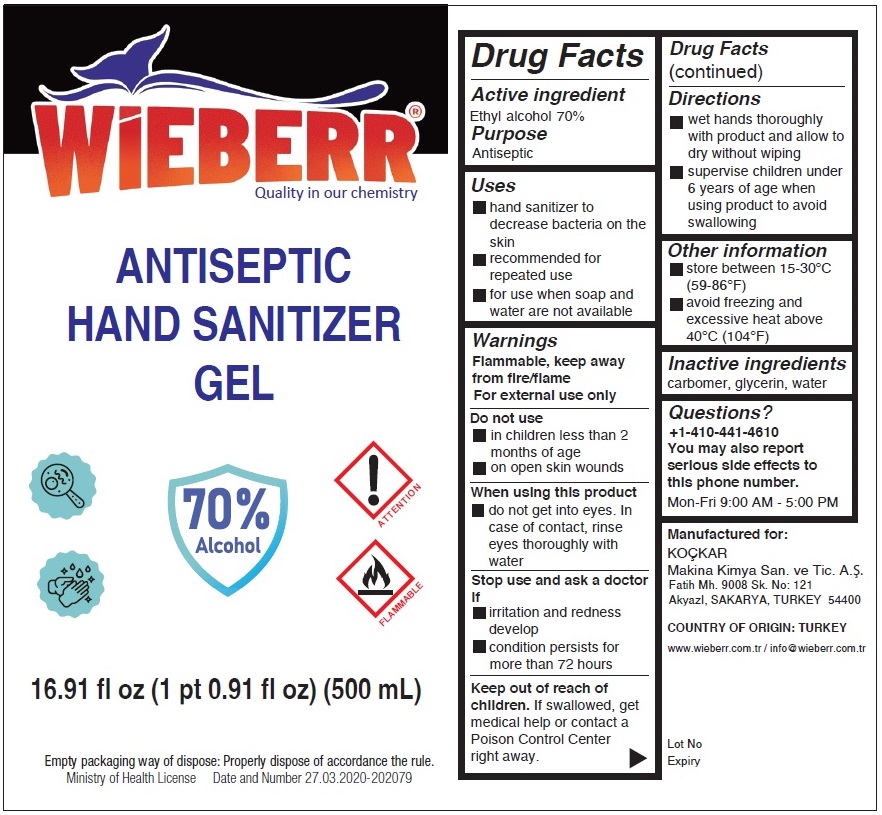 DRUG LABEL: ANTISEPTIC HAND SANITIZER
NDC: 78433-101 | Form: GEL
Manufacturer: KOCKAR MAKINA KIMYA SANAYI VE TICARET ANONIM SIRKETI
Category: otc | Type: HUMAN OTC DRUG LABEL
Date: 20200707

ACTIVE INGREDIENTS: ALCOHOL 70 mL/100 mL
INACTIVE INGREDIENTS: CARBOMER HOMOPOLYMER, UNSPECIFIED TYPE; GLYCERIN; WATER

WIEBERR® ANTISEPTIC HAND SANITIZER GEL

Active ingredient

Ethyl alcohol 70%

Purpose

Antiseptic

Uses

▪ hand sanitizer to decrease bacteria on the skin

▪ recommended for repeated use

▪ for use when soap and water are not available

Warnings

Flammable, keep away from fire/flame

For external use only

Do not use

▪ in children less than 2 months of age

▪ on open skin wounds

When using this product

▪ do not get into eyes. In case of contact, rinse eyes thoroughly with water.

Stop use and ask a doctor if

▪ irritation and redness develop

▪ condition persists for more than 72 hours

Keep out of reach of children. If swallowed, get medical help or contact a Poison Control Center right away.

Directions

▪ wet hands thoroughly with product and allow to dry without wiping

▪ supervise children under 6 years of age when using this product to avoid swallowing

Other information

▪ store between 15-30°C (59-86°F)

▪ avoid freezing and excessive heat above 40°C (104°F)

Inactive ingredients

carbomer, glycerin, water

Questions?

+1-410-441-4610

You may also report serious side effects to this phone number.

Mon-Fri 9:00 AM - 5:00 PM

Quality in our chemistry

Empty packaging way of dispose: Properly dispose of accordance the rule.

Ministry of Health License Date and Number 27.03.2020-202079

Manufactured for:

KOÇKAR

Makina Kimya San. ve Tic. A.S.

Fatih Mh. 9008 Sk. No: 121

AkyazI, SAKARYA, TURKEY 54400

COUNTRY OF ORIGIN: TURKEY

www.wieberr.com.tr / info@wieberr.com.tr